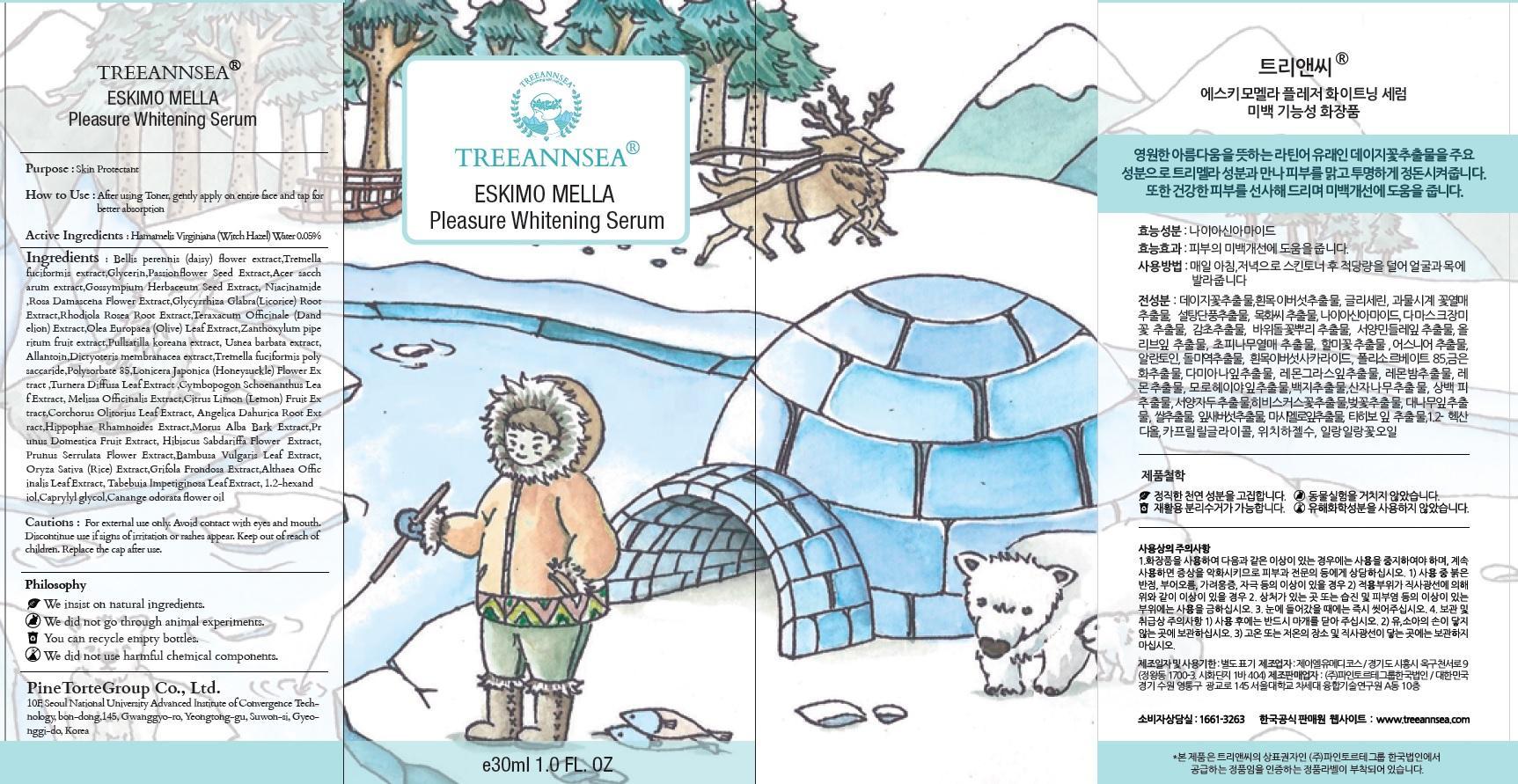 DRUG LABEL: TREEANNSEA ESKIMO MELLA PLEASURE WHITENING SERUM
NDC: 69515-020 | Form: CREAM
Manufacturer: PINE TORTE GROUP CO., LTD.
Category: otc | Type: HUMAN OTC DRUG LABEL
Date: 20150318

ACTIVE INGREDIENTS: Witch Hazel 0.015 mg/30 mL
INACTIVE INGREDIENTS: Glycerin; Niacinamide

ACTIVE INGREDIENT

Active Ingredients: Hamamelis Virginiana (Witch Hazel) Water 0.05%

INACTIVE INGREDIENT

Inactive Ingredients: Bellis perennis (daisy) flower extract, Tremella fuciformis extract, Glycerin, Passionflower Seed Extract, Acer saccharum extract, Gossympium Herbaceum Seed Extract, Niacinamide, Rosa Damascena Flower Extract, Glycyrrhiza Glabra(Licorice) Root Extract, Rhodiola Rosea Root Extract, Teraxacum Officinale (Dandelion) Extract, Olea Europaea (Olive) Leaf Extract, Zanthoxylum piperitum fruit extract/Pullsatilla koreana extract, Usnea barbata extract, Allantoin, Dictyoteris membranacea extract, Tremella fuciformis polysaccaride, Polysorbate 85, Lonicera Japonica (Honeysuckle) Flower Extract, Turnera Diffusa Leaf Extract, Cymbopogon Schoenanthus Leaf Extract, Melissa Officinalis Extract, Citrus Limon (Lemon) Fruit Extract, Corchorus Olitorius Leaf Extract, Angelica Dahurica Root Extract, Hippophae Rhamnoides Extract, Morus Alba Bark Extract, Prunus Domestica Fruit Extract, Hibiscus Sabdariffa Flower Extract, Prunus Serrulata Flower Extract, Bambusa Vulgaris Leaf Extract, Oryza Sativa (Rice) Extract, Grifola Frondosa Extract, Althaea Officinalis Leaf Extract, Tabebuia Impetiginosa Leaf Extract, 1,2-hexandiol, Caprylyl glycol, Canange odorata flower oil

PURPOSE

Purpose: Skin Protectant

Cautions

Cautions: For external use only. Avoid contact with eyes and mouth. Discountinue use if signs of irritation or rashes appear. Keep out of reach of children. Replace the cap after use.

KEEP OUT OF REACH OF CHILDREN

INDICATIONS & USAGE

How to use: After using Toner, gently apply on entire face and tap for better absorption.

DOSAGE & ADMINISTRATION

How to use: After using Toner, gently apply on entire face and tap for better absorption.